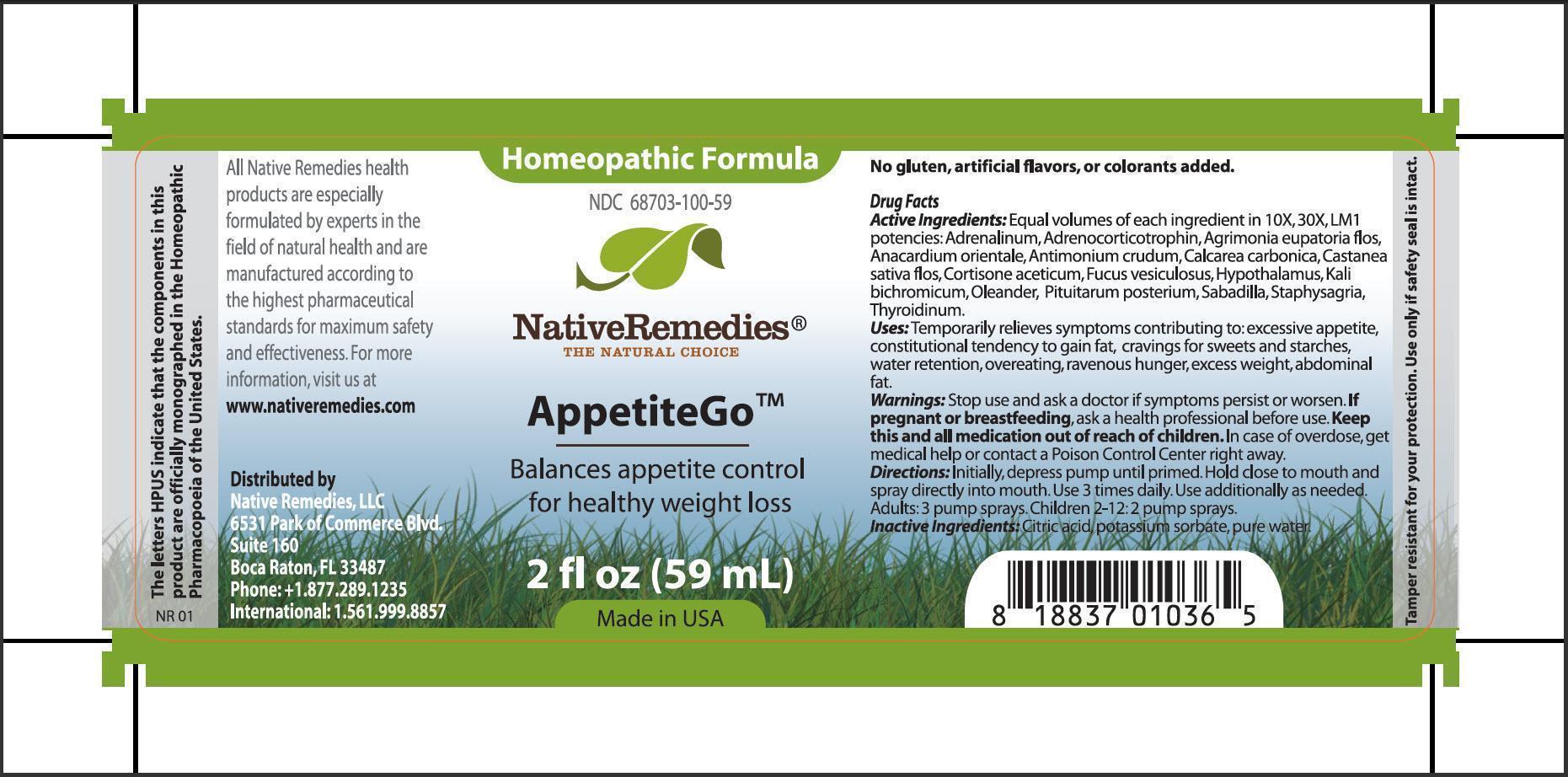 DRUG LABEL: AppetiteGo
NDC: 68703-100 | Form: SPRAY
Manufacturer: Silver Star Brands
Category: homeopathic | Type: HUMAN OTC DRUG LABEL
Date: 20150716

ACTIVE INGREDIENTS: EPINEPHRINE 10 [hp_X]/59 mL; CORTICOTROPIN 10 [hp_X]/59 mL; AGRIMONIA EUPATORIA FLOWER 10 [hp_X]/59 mL; SEMECARPUS ANACARDIUM JUICE 10 [hp_X]/59 mL; ANTIMONY TRISULFIDE 10 [hp_X]/59 mL; OYSTER SHELL CALCIUM CARBONATE, CRUDE 10 [hp_X]/59 mL; CASTANEA SATIVA FLOWER 10 [hp_X]/59 mL; CORTISONE ACETATE 10 [hp_X]/59 mL; FUCUS VESICULOSUS 10 [hp_X]/59 mL; BOS TAURUS HYPOTHALAMUS 10 [hp_X]/59 mL; POTASSIUM DICHROMATE 10 [hp_X]/59 mL; NERIUM OLEANDER LEAF 10 [hp_X]/59 mL; SUS SCROFA PITUITARY GLAND 10 [hp_X]/59 mL; SCHOENOCAULON OFFICINALE SEED 10 [hp_X]/59 mL; DELPHINIUM STAPHISAGRIA SEED 10 [hp_X]/59 mL; THYROID, UNSPECIFIED 10 [hp_X]/59 mL
INACTIVE INGREDIENTS: CITRIC ACID MONOHYDRATE; POTASSIUM SORBATE; WATER

AppetiteGo

PURPOSE

Balances appetite control for healthy weight loss

Drug Facts
Active Ingredients : Equal volumes of each ingredient in 10X, 30X, LM1 potencies: Adrenalinum, Adrenocorticotrophin, Agrimonia eupatoria flos, Anacardium orientale, Antimonium crudum, Clacarea carbonica, Castanea sativa flos, Cortisone aceticum, Fucus vesiculosus, Hypothalamus, Kali buchromicum, Oleander, Pituitarum posterium, Sabadilla, Staphysagria, Thyroidinum

INDICATIONS AND USAGE

Uses: Temporarily relieves symptoms contributing to excessive appetite, constitutional tendency to gain fat, cravings for sweets and starches, water retention, overeating, ravenous hunger, excess weight, abdominal fat

WARNINGS

Warnings: Stop use and ask a doctor if symptoms persist or worsen

PREGNANCY OR BREAST FEEDING

If pregnant or breastfeeding, ask a health professional before use

KEEP OUT OF REACH OF CHILDREN

Keep this and all medication out of reach of children

OVERDOSAGE

In case of overdose, get medical help or contact a Poison Control Center right away

DOSAGE AND ADMINISTRATION

Directions: Initially, depress pump until primed. Hold close to mouth and spray directly into mouth. Use 3 times daily. Use additionally as needed. Adults: 3 pump sprays. Children 2-12:2 pump sprays

Inactive Ingredients: Citric acid, potassium sorbate, pure water

PATIENT COUNSELING INFORMATION

The letters HPUS indicate that the components in this product are officially monographed in the Homeopathic Pharmacopoeia of the United States.

All Native Remedies health products are especially formulated by experts in the field of natural health and are manufactured according to the highest pharmaceutical standards for maximum safety and effectiveness. For more information, visit us at www.nativeremedies.com

Distributed by
Native Remedies, LLC
6531 Park of Commerce Blvd.
Suite 160
Boca Raton, Fl 33487
Phone:+1.877.289.1235
International:1.561.999.8857

No gluten, artificial flavors, or colorants added

STORAGE AND HANDLING

Tamper resistant for your protection. Use only if safety seal is intact